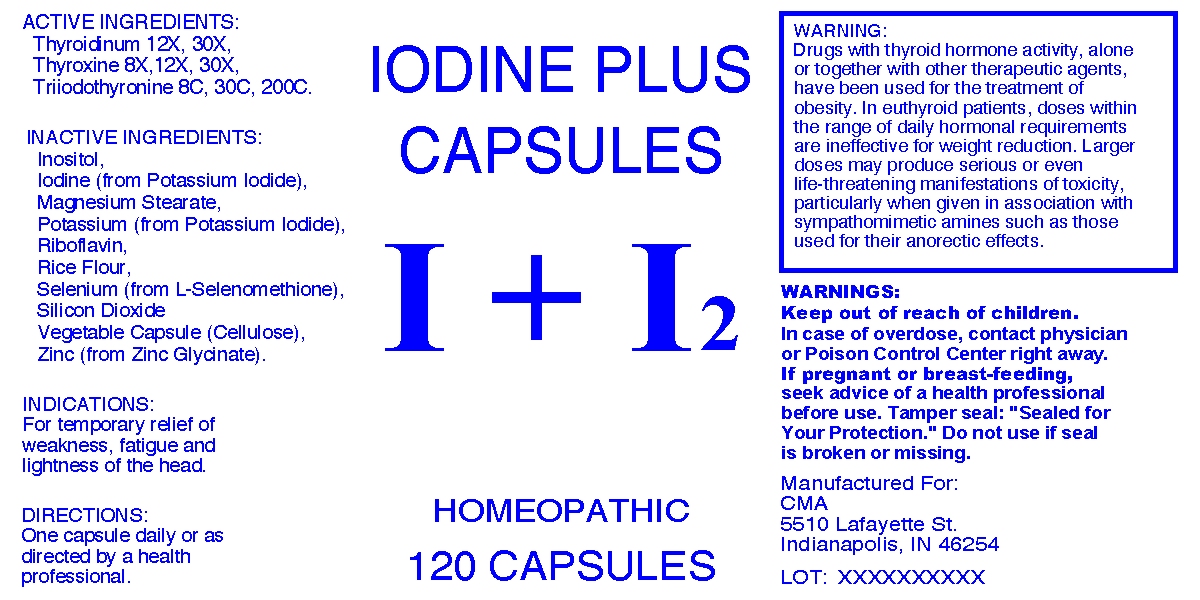 DRUG LABEL: Iodine Plus Capsule
NDC: 57520-0154 | Form: CAPSULE
Manufacturer: Apotheca Company
Category: homeopathic | Type: HUMAN OTC DRUG LABEL
Date: 20100713

ACTIVE INGREDIENTS: THYROID 30 [hp_X]/1 mg; LEVOTHYROXINE 30 [hp_X]/1 mg; LIOTHYRONINE 200 [hp_C]/1 mg
INACTIVE INGREDIENTS: INOSITOL; POTASSIUM IODIDE; MAGNESIUM STEARATE; RIBOFLAVIN; RICE; SELENOMETHIONINE; SILICON DIOXIDE; POWDERED CELLULOSE; ZINC

Iodine Plus Capsules

ACTIVE INGREDIENT

ACTIVE INGREDIENTS: Thyroidinum 12X, 30X, Thyroxine 8X, 12X, 30X, Triiodothyronine 8C, 30C, 200C.

PURPOSE

INDICATIONS: For temporary relief of weakness, fatigue and lightness of the head.

WARNINGS

WARNINGS: Keep out of reach of children. In case of overdose, contact physician or Poison Control Center right away. If pregnant or breast-feeding, seek advice of a health professional before use. Tamper seal: "Sealed for your protection." Do not use if seal is broken or missing.

WARNING: Drugs with thyroid hormone activity, alone or together with other therapeutic agents, have been used for the treatment of obesity. In euthyroid patients, doses within the range of daily hormonal requirements are ineffective for weight reduction. Larger doses may produce serious or even life-threatening manifestations of toxicity, particularly when given in association with sympathomimetic amines such as those used for their anorectic effects.

DOSAGE AND ADMINISTRATION

DIRECTIONS: One capsule daily or as directed by a health professional.

INACTIVE INGREDIENT

INACTIVE INGREDIENTS: Inositol, Iodine (from Potassium Iodide), Magnesium stearate, Potassium (from Potassium Iodide), Riboflavin, Rice flour, Selenium (from L-selenomethione), Silicon dioxide, Vegetable capsule (cellulose), Zinc (from Zinc Glycinate).

QUESTIONS

Manufactured For:

CMA

5510 Lafayette St.

Indianapolis, IN 46254

PACKAGE LABEL

IODINE PLUS CAPSULES

I + I 2

HOMEOPATHIC

120 CAPSULES